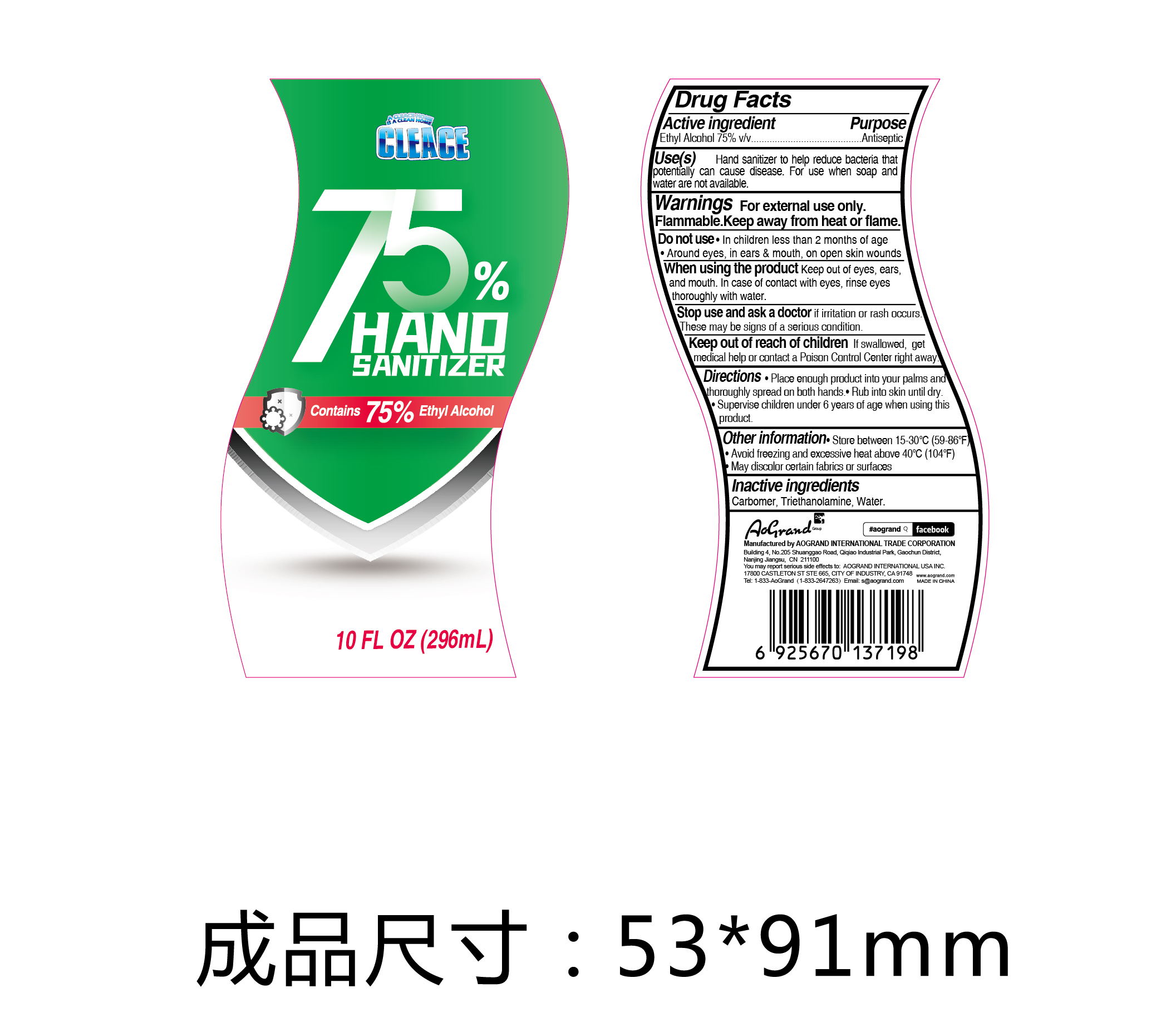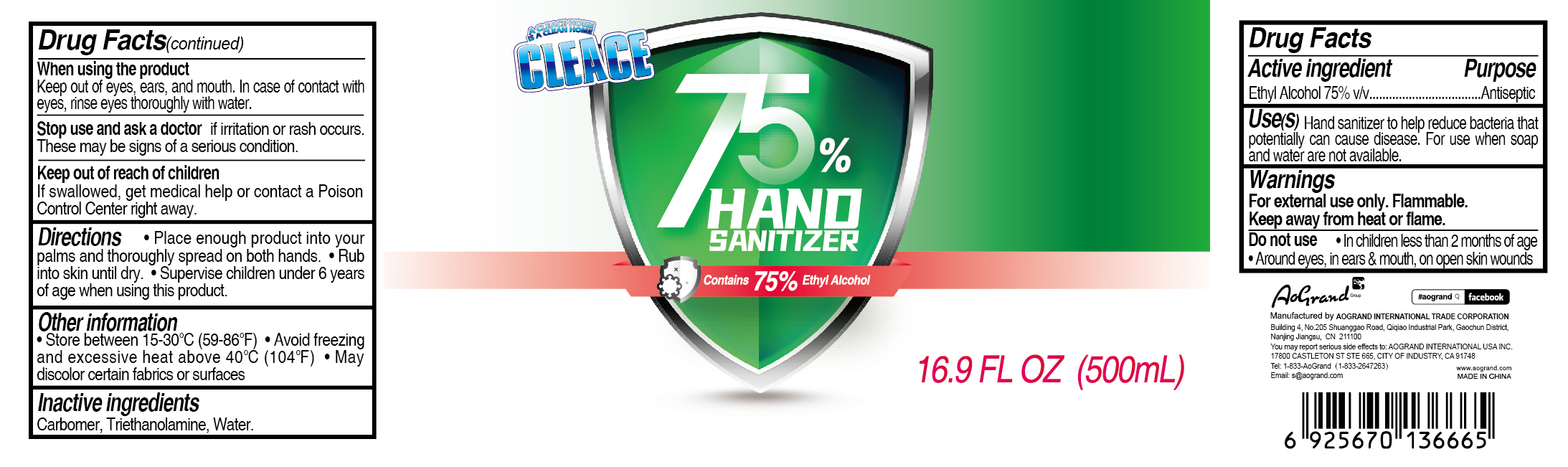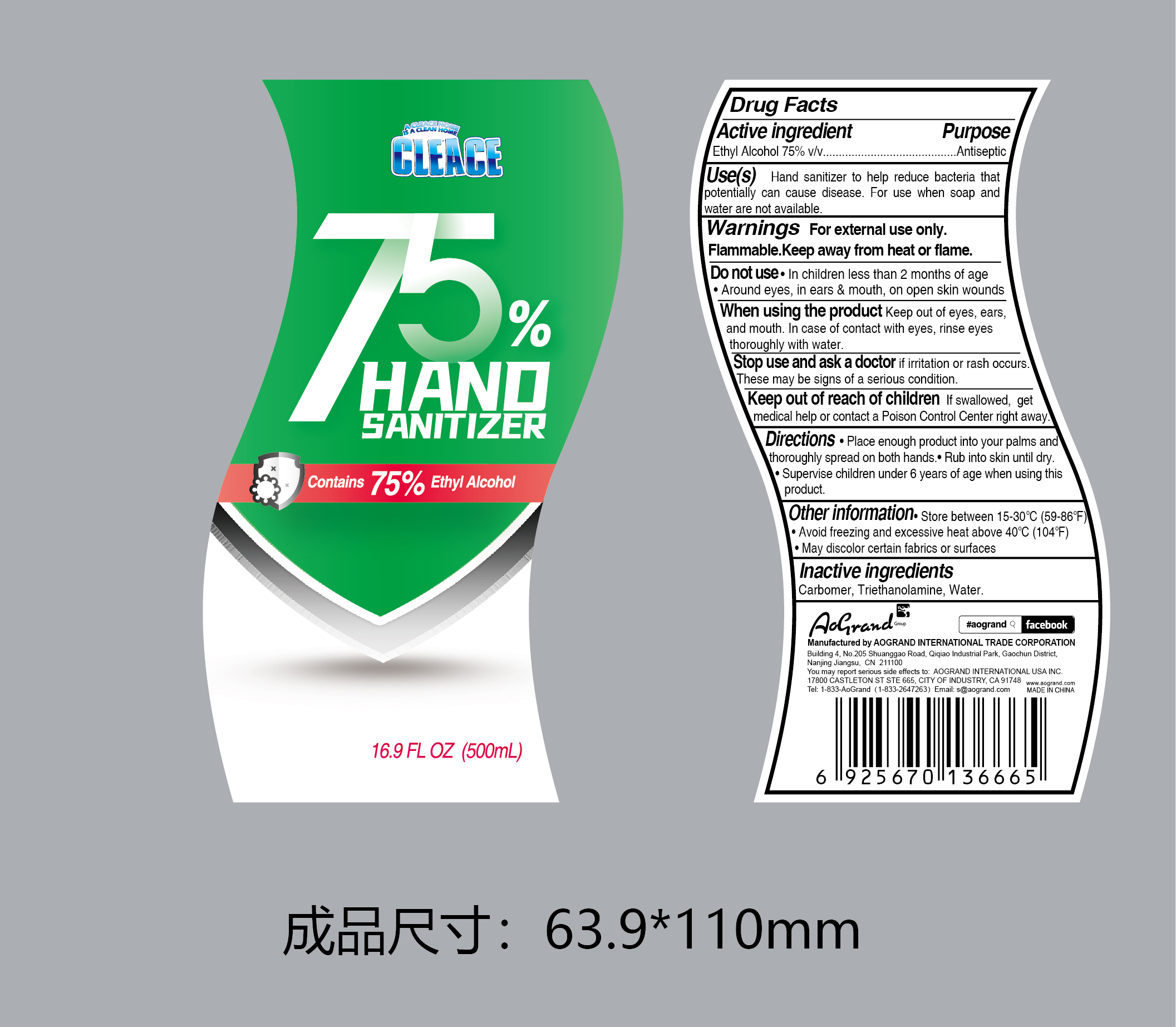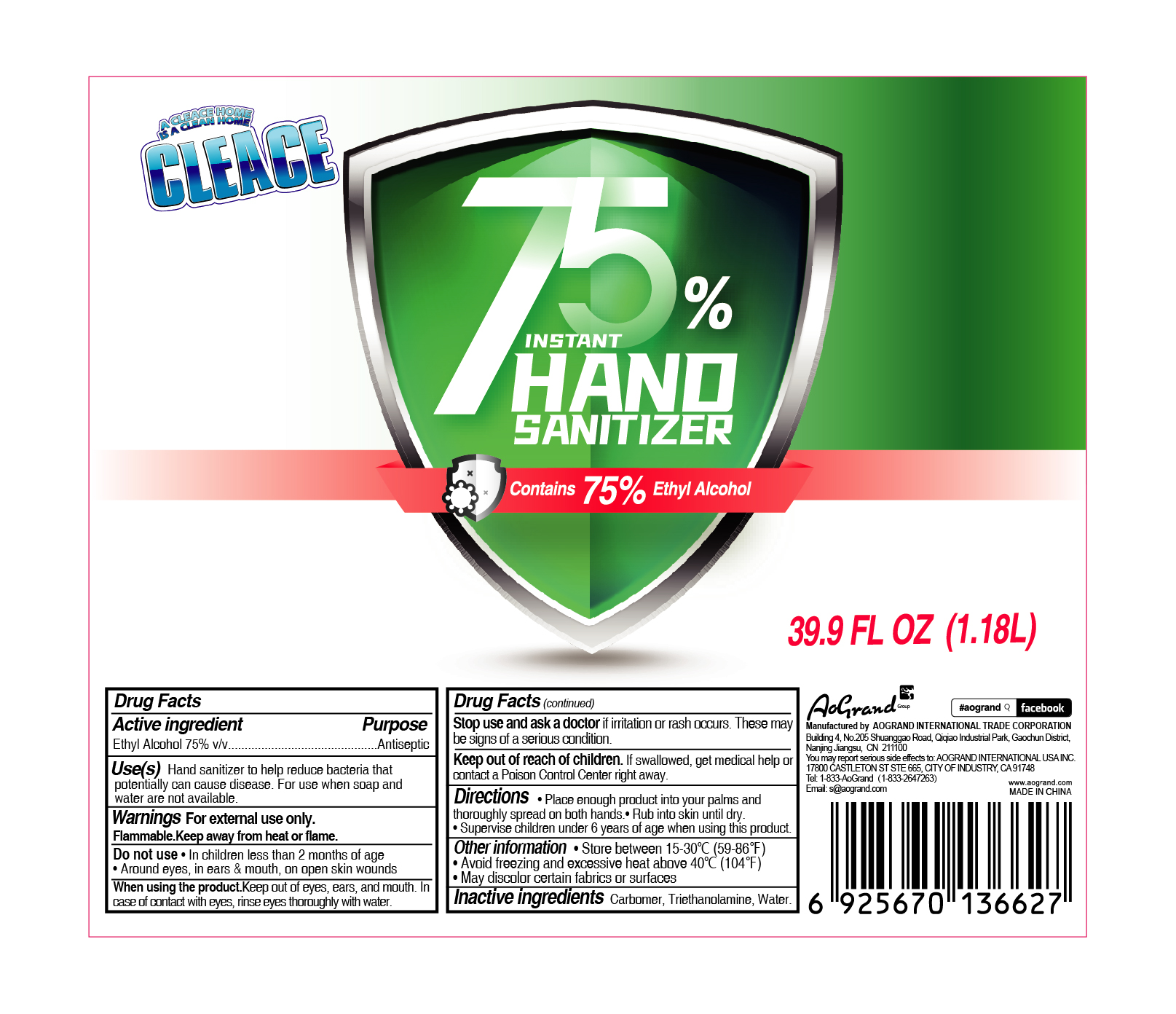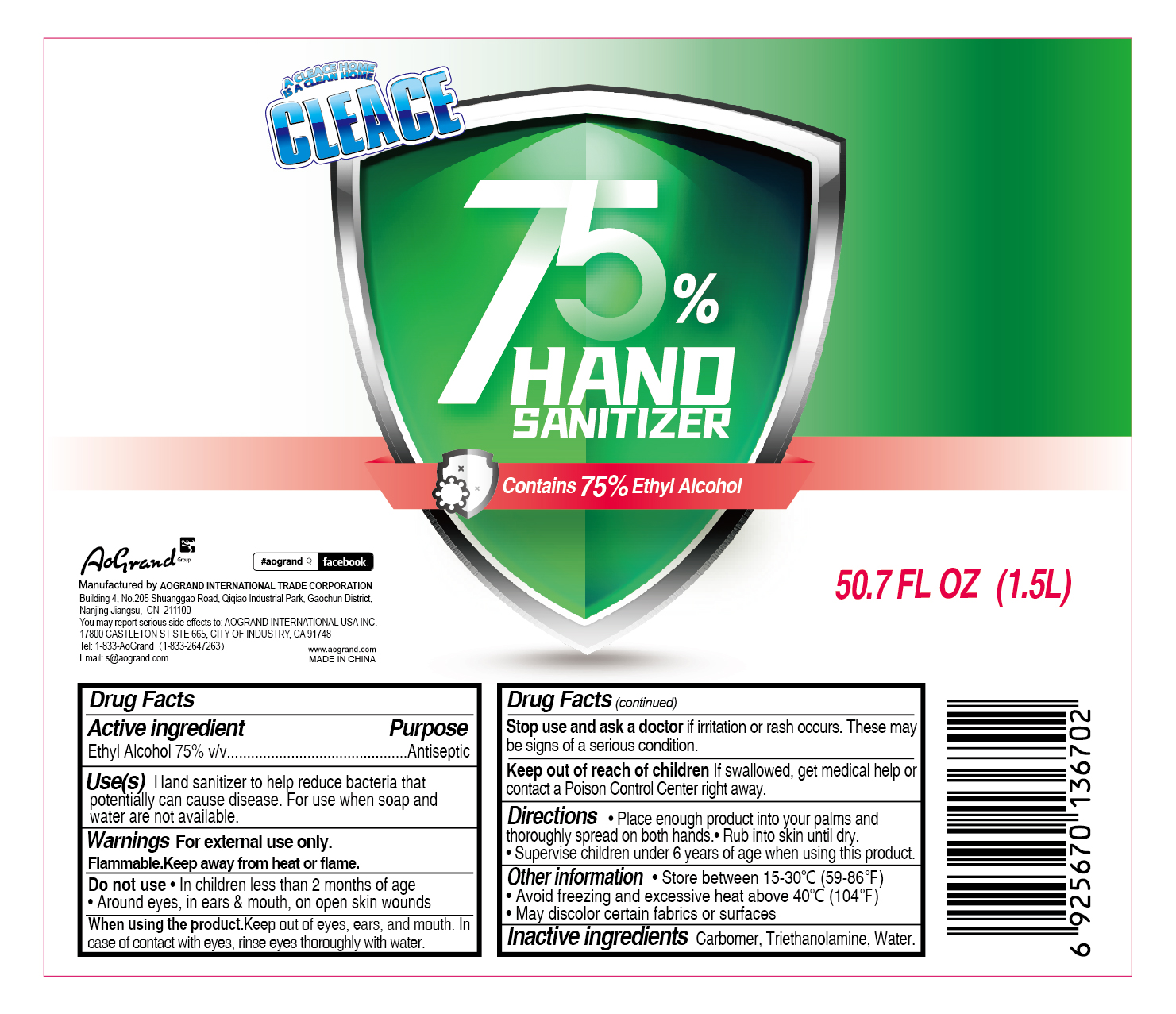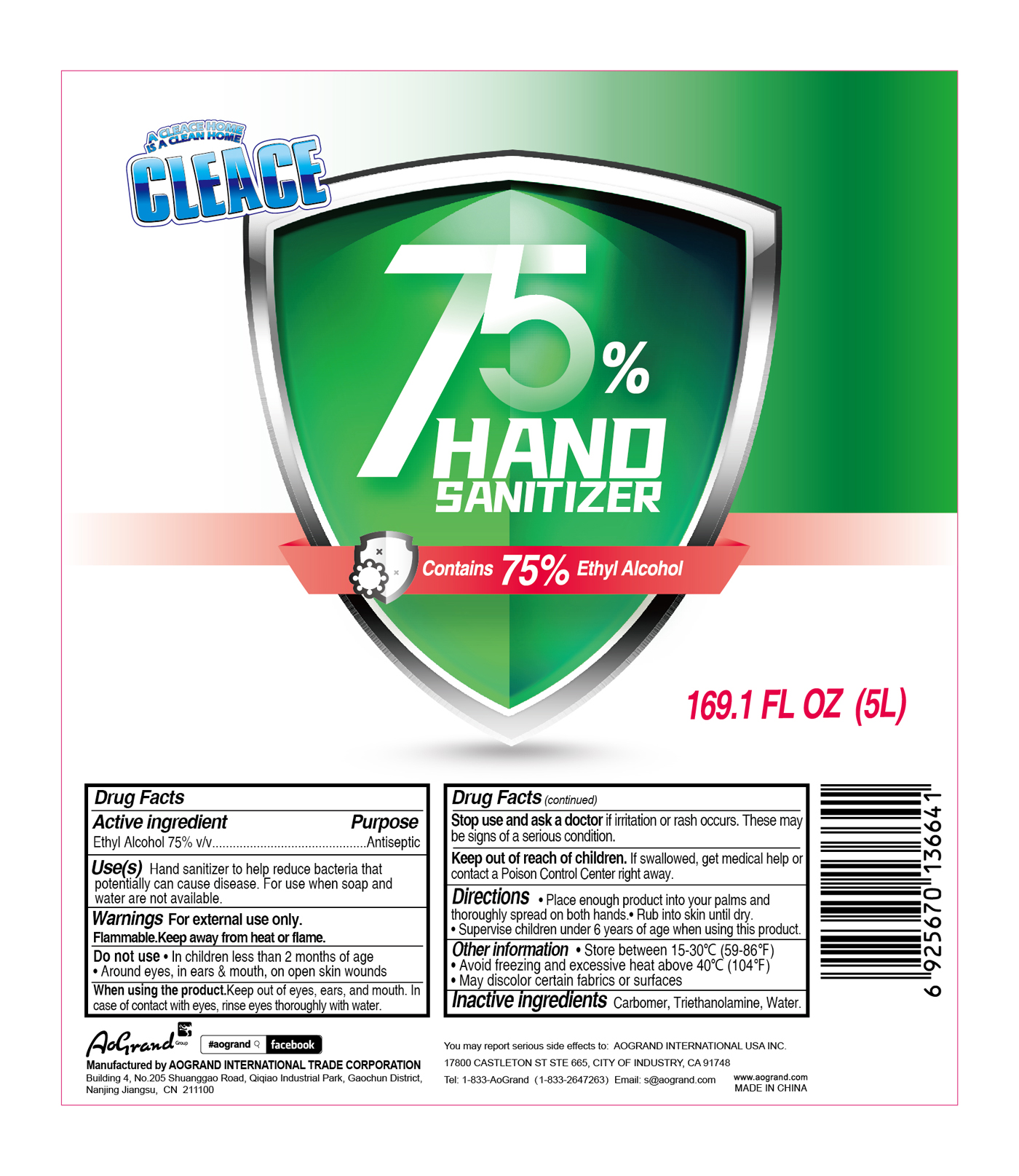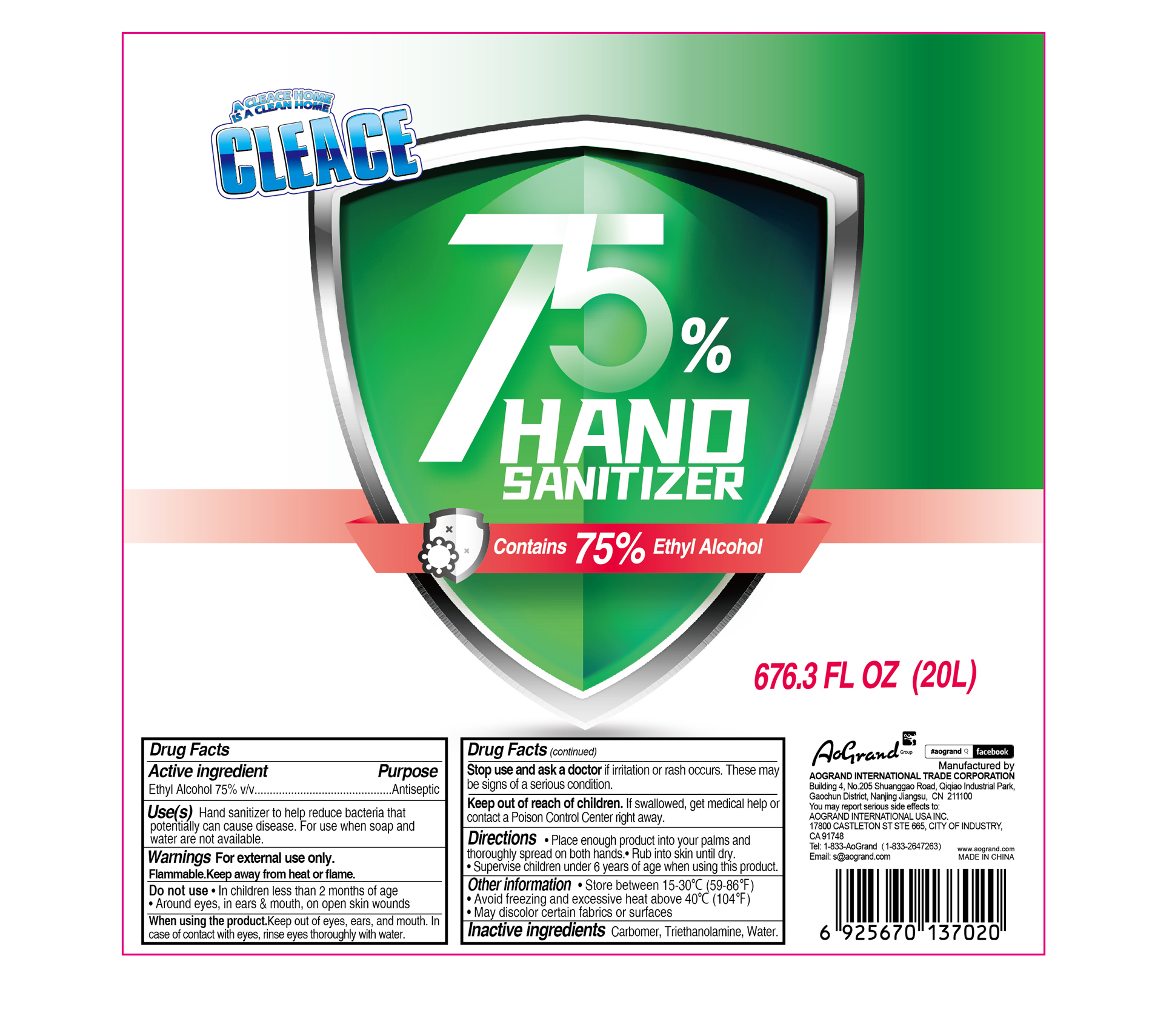 DRUG LABEL: CLEACE 75% Alcohol hand sanitizer
NDC: 74621-024 | Form: GEL
Manufacturer: Aogrand International Trade Corporation
Category: otc | Type: HUMAN OTC DRUG LABEL
Date: 20230211

ACTIVE INGREDIENTS: ALCOHOL 75 mL/100 mL
INACTIVE INGREDIENTS: CARBOMER HOMOPOLYMER, UNSPECIFIED TYPE; WATER; TROLAMINE

CLEACE 75% Alcohol hand sanitizer

Active Ingredient

Ethyl Alcohol 75% v/v Antiseptic

Purpose

Antiseptic, Hand Sanitizer

Use(s)

Hand sanitizer to help reduce bacteria that potentially can cause disease. For use when soap and water are not available.

Warnings

For external use only. Flammable.

Keep away from fire or flame.

Do not use

- in children less than 2 months of age.
- Around eyes, in ears & mouth, on open skin wounds

When using this product

Keep out of eyes, ears, and mouth. In case of contact with eyes, rinse eyes thoroughly with water

Stop use and ask a doctor

if irritation or rash occurs. These may be signs of a serious condition

Keep out of reach of children.

if swallowed, get medical help or contact a Poison Control Center right away.

Directions

- Place enough product into your palms and thoroughly spread on both hands.
- Rub into skin until dry.
- Supervise children under 6 years of age when using this product.

Other information

- Store between 15-30C (59-86F)
- Avoid freezing and excessive heat above 40C (104F)
- May discolor certain fabrics or surfaces.

Inactive ingredients

carbomer, triethanolamine, water

Package Label - Principal Display Panel

296mL NDC: 74621-024-01

A CLEACE HOME

IS A CLEAN HOME

CLEACE

75%

Hand Sanitizer

Contain 75% Ethyl Alcohol

10 FL OZ (296mL)

500mL NDC: 74621-024-02

A CLEACE HOME

IS A CLEAN HOME

CLEACE

75%

Hand Sanitizer

Contain 75% Ethyl Alcohol

16.9 FL OZ (500mL)

500mL NDC: 74621-024-03

A CLEACE HOME

IS A CLEAN HOME

CLEACE

75%

Hand Sanitizer

Contain 75% Ethyl Alcohol

16.9 FL OZ (500mL)

1180mL NDC: 74621-024-04

A CLEACE HOME

IS A CLEAN HOME

CLEACE

75%

Hand Sanitizer

Contain 75% Ethyl Alcohol

39.9 FL OZ (1.18L)

1500mL NDC: 74621-024-05

A CLEACE HOME

IS A CLEAN HOME

CLEACE

75%

Hand Sanitizer

Contain 75% Ethyl Alcohol

50.7 FL OZ (1.5L)

5000mL NDC: 74621-024-06

A CLEACE HOME

IS A CLEAN HOME

CLEACE

75%

Hand Sanitizer

Contain 75% Ethyl Alcohol

169.1 FL OZ (5L)

20000mL NDC: 74621-024-07

A CLEACE HOME

IS A CLEAN HOME

CLEACE

75%

Hand Sanitizer

Contain 75% Ethyl Alcohol

676.3 FL OZ (20L)